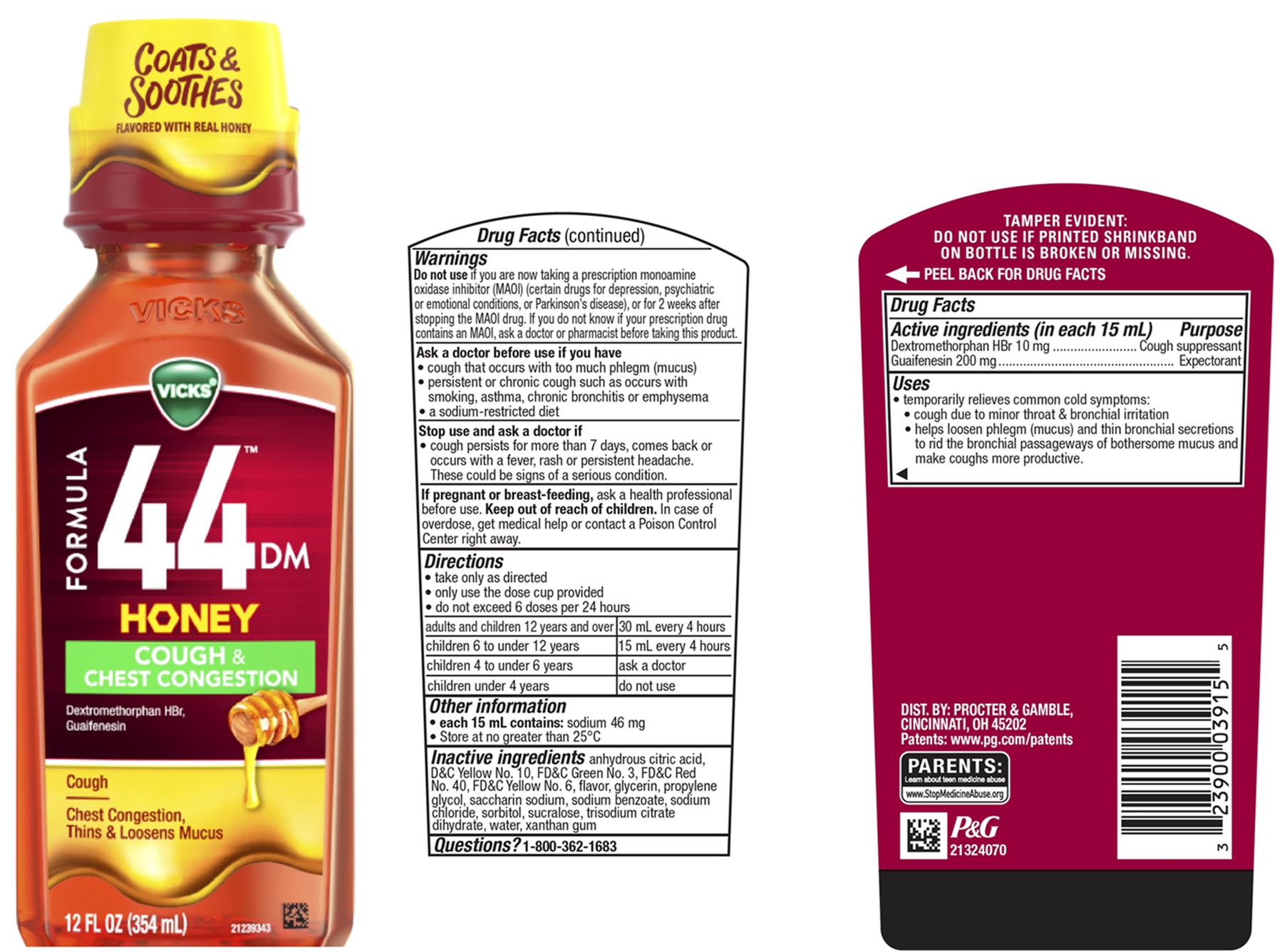 DRUG LABEL: Vicks Formula 44DM
NDC: 84126-355 | Form: LIQUID
Manufacturer: The Procter & Gamble Manufacturing Company
Category: otc | Type: HUMAN OTC DRUG LABEL
Date: 20250409

ACTIVE INGREDIENTS: DEXTROMETHORPHAN HYDROBROMIDE 20 mg/30 mL; GUAIFENESIN 400 mg/30 mL
INACTIVE INGREDIENTS: SODIUM CHLORIDE; GLYCERIN; SODIUM BENZOATE; SORBITOL; XANTHAN GUM; PROPYLENE GLYCOL; WATER; SACCHARIN SODIUM; FD&C RED NO. 40; CITRIC ACID; D&C YELLOW NO. 10; FD&C GREEN NO. 3; FD&C YELLOW NO. 6; SUCRALOSE; TRISODIUM CITRATE DIHYDRATE

Vicks® Formula 44TM DM Cough & Congestion Honey Flavored Liquid

Drug Facts

Active ingredients (in each 15 mL)

Dextromethorphan HBr 10 mg
Guaifenesin 200 mg

Purpose

Cough suppressant
Expectorant

Uses

- temporarily relieves common cold symptoms:

• cough due to minor throat & bronchial irritation

• helps loosen phlegm (mucus) and thin bronchial secretions to rid the bronchial passageways of bothersome mucus and make coughs

more productive.

Warnings

Do not use

if you are now taking a prescription monoamine oxidase inhibitor (MAOI) (certain drugs for depression, psychiatric or emotional conditions, or Parkinson's disease), or for 2 weeks after stopping the MAOI drug. If you do not know if your prescription drug contains an MAOI, ask a doctor or pharmacist before taking this product.

Ask a doctor before use if you have

- cough that occurs with too much phlegm (mucus)
- persistent or chronic cough such as occurs with smoking, asthma, chronic bronchitis or emphysema
- a sodium-restricted diet

Stop use and ask a doctor if

- cough persists for more than 7 days, comes back or occurs with a fever, rash or persistent headache.
  These could be signs of a serious condition.

If pregnant or breast-feeding,

ask a health professional before use.

Keep out of reach of children.

In case of overdose, get medical help or contact a Poison Control Center right away.

Directions

• take only as directed
• only use the dose cup provided
• do not exceed 6 doses per 24 hours

adults & children 12 yrs & over | 30 mL every 4 hrs
children 6 to under 12 yrs | 15 mL every 4 hrs
children 4 to under 6 yrs | ask a doctor
children under 4 yrs | do not use

Other information

• each 15 mL contains: sodium 46 mg

• store at no greater than 25°C

Inactive ingredients

anhydrous citric acid, D&C Yellow No. 10, FD&C Green No. 3, FD&C Red No. 40, FD&C Yellow No. 6, flavor, glycerin, propylene glycol, saccharin sodium, sodium benzoate, sodium chloride, sorbitol, sucralose, trisodium citrate dihydrate, water, xanthan gum

Questions?

1-800-362-1683

TAMPER EVIDENT: DO NOT USE IF PRINTED SHRINKBAND ON BOTTLE IS BROKEN OR MISSING.

PRINCIPAL DISPLAY PANEL - 354 ml Bottle Label

VICKS®

FORMULA 44DM

HONEY COUGH & CONGESTION

Dextromethorphan HBr

Guaifenesin

Cough

Chest Congestion, Thins & Loosens Mucus

12 FL OZ (354 mL)